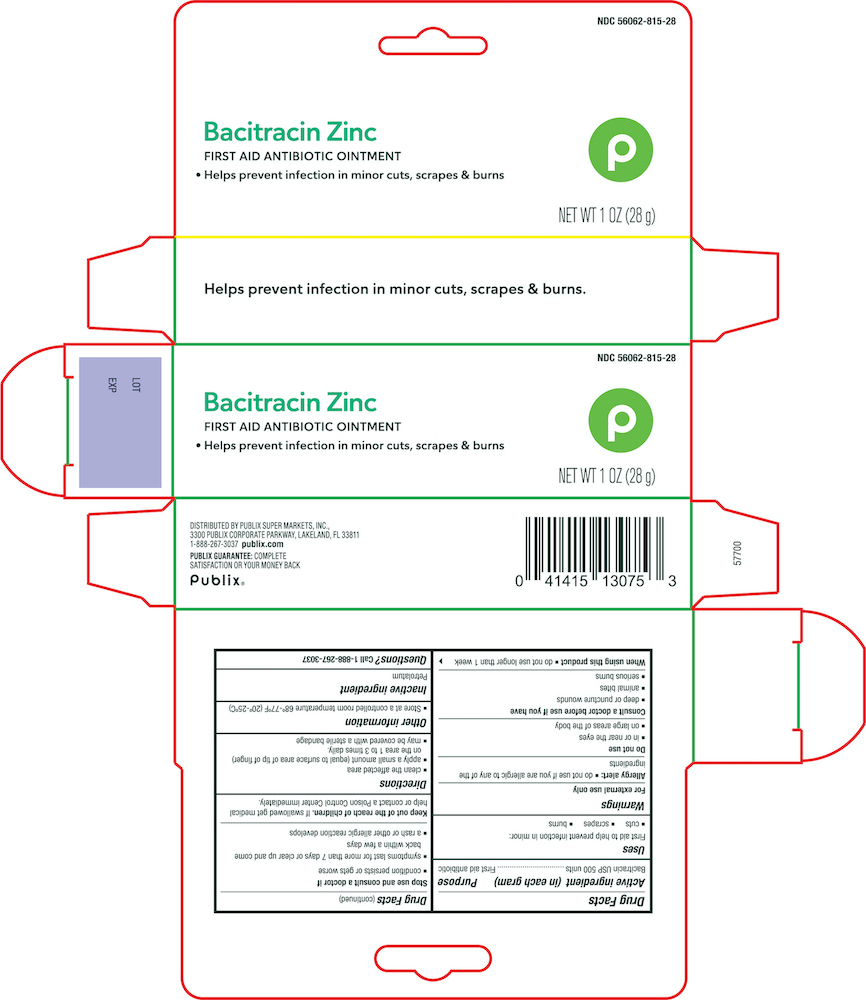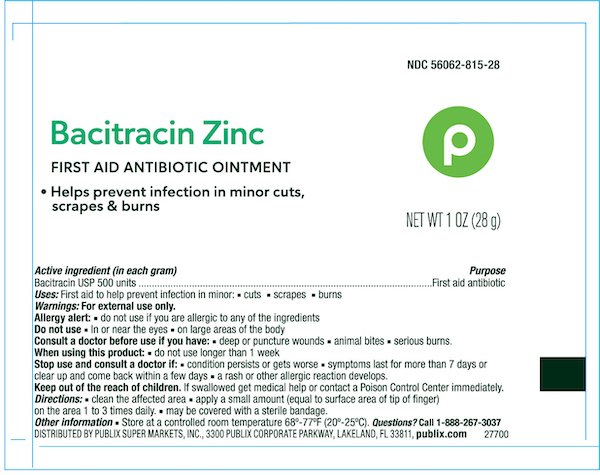 DRUG LABEL: Publix Bacitracin Zinc
NDC: 56062-815 | Form: OINTMENT
Manufacturer: PUBLIX SUPER MARKETS, INC.
Category: otc | Type: HUMAN OTC DRUG LABEL
Date: 20240617

ACTIVE INGREDIENTS: BACITRACIN ZINC 500 [USP'U]/1 g
INACTIVE INGREDIENTS: PETROLATUM

Publix Bacitracin Zinc Ointment

Active ingredient

Bacitracin Zinc 500 USP Units/gram

Purpose

First aid antibiotic

Uses

First aid to help prevent infection in minor:

- cuts
- scrapes
- burns

Warnings

For external use only

Allergy Alert

- do not use if you are allergic to any of the ingredients

When using this product

- do not use longer than 1 week

Do not use

- in or near the eyes
- on large areas of the body

Consult a doctor before use if you have;

- deep or puncture wounds
- animal bites
- serious burns

Stop use and consult a doctor if

- condition persists or gets worse
- symptoms last for more than 7 days or clear up and come back within a few days
- a rash or other allergic reaction develops

Directions

- clean the affected area
- apply a small amount (equal to surface area of tip of finger) on the area 1 to 3 times daily.
- may be covered with a sterile bandage

Other information

- Store at a controlled room temperature 20º-25ºC (68° to 77°F)

Inactive ingredient

Petrolatum

Principal display panel

Publix Bacitracin Zinc 56062-815-28

First aid antibiotic ointment

NET WT 1 OZ (28g)